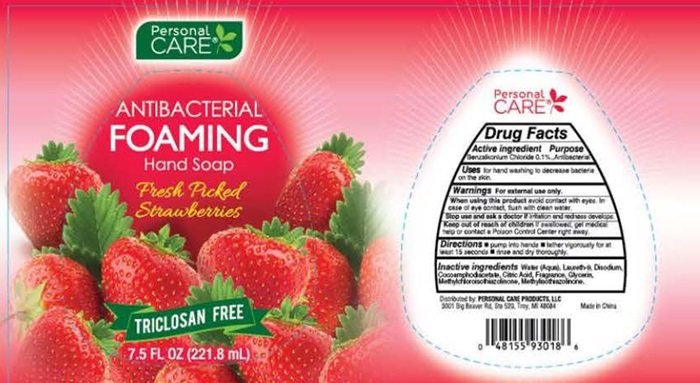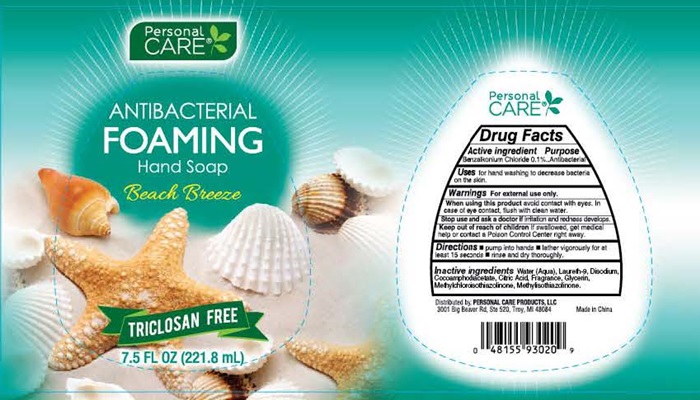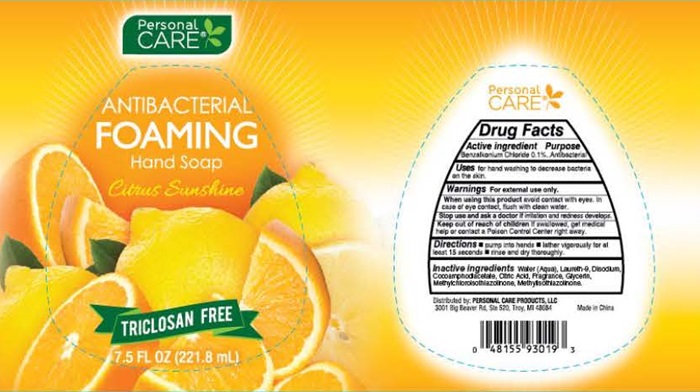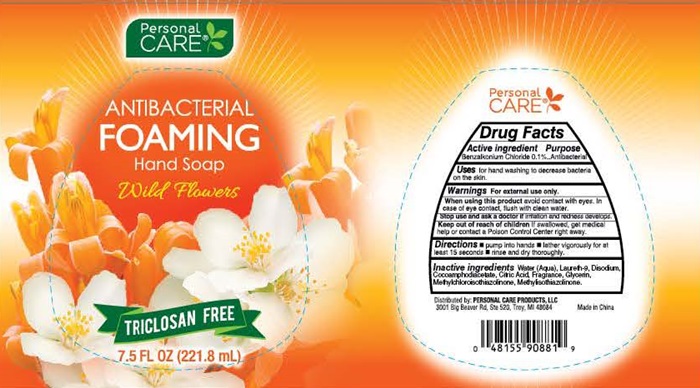 DRUG LABEL: Personal CARE Antibacterial
NDC: 29500-9881 | Form: LIQUID
Manufacturer: Personal Care Products, LLC
Category: otc | Type: HUMAN OTC DRUG LABEL
Date: 20151210

ACTIVE INGREDIENTS: BENZALKONIUM CHLORIDE 0.0002218 mg/221.8 mL
INACTIVE INGREDIENTS: WATER; LAURETH-9; DISODIUM COCOAMPHODIACETATE; CITRIC ACID MONOHYDRATE; GLYCERIN; METHYLCHLOROISOTHIAZOLINONE; METHYLISOTHIAZOLINONE

Personal CARE Antibacterial Foaming Hand Soap
Wild Flowers - Fresh Picked Strawberries - Beach Breeze - Citrus Sunshine

Drug Facts Active ingredient

Benzalkonium Chloride 0.1%

Purpose

Antibacterial

Keep out of reach of children. If swallowed, get medical help or contact a Poison Control Center right away.

Uses

for hand washing to decrease bacteria on the skin.

Warnings

For external use only.

When using this product

avoid contact with eyes. In case of eye contact, flush with clean water.

Stop use and ask a doctor

if irritation and redness develops.

Directions

- pump into hands
- lather vigorously for at least 15 seconds
- rinse and dry thoroughly.

Inactive ingredients

Water (Aqua), Laureth-9, Disodium, Cocoamphodiacetate, Citric Acid, Fragrance, Glycerin, Methylchloroisothiazolinone, Methylisothiazolinone.

Personal CARE ® ANTIBACTERIAL FOAMING Hand Soap Labels Wild Flowers Fresh Picked Strawberries Breach Breeze Citrus Sunshine

Personal CARE ® ANTIBACTERIAL FOAMING Hand Soap

Wild Flowers
Fresh Picked Strawberries
Breach Breeze
Citrus Sunshine

TRICLOSAN FREE
7.5 FL OZ (221.8 mL)

Distributed by: PERSONAL CARE PRODUCTS, LLC

3001 Big Beaver Rd, Ste 520 Troy, MI 43034

Made in China